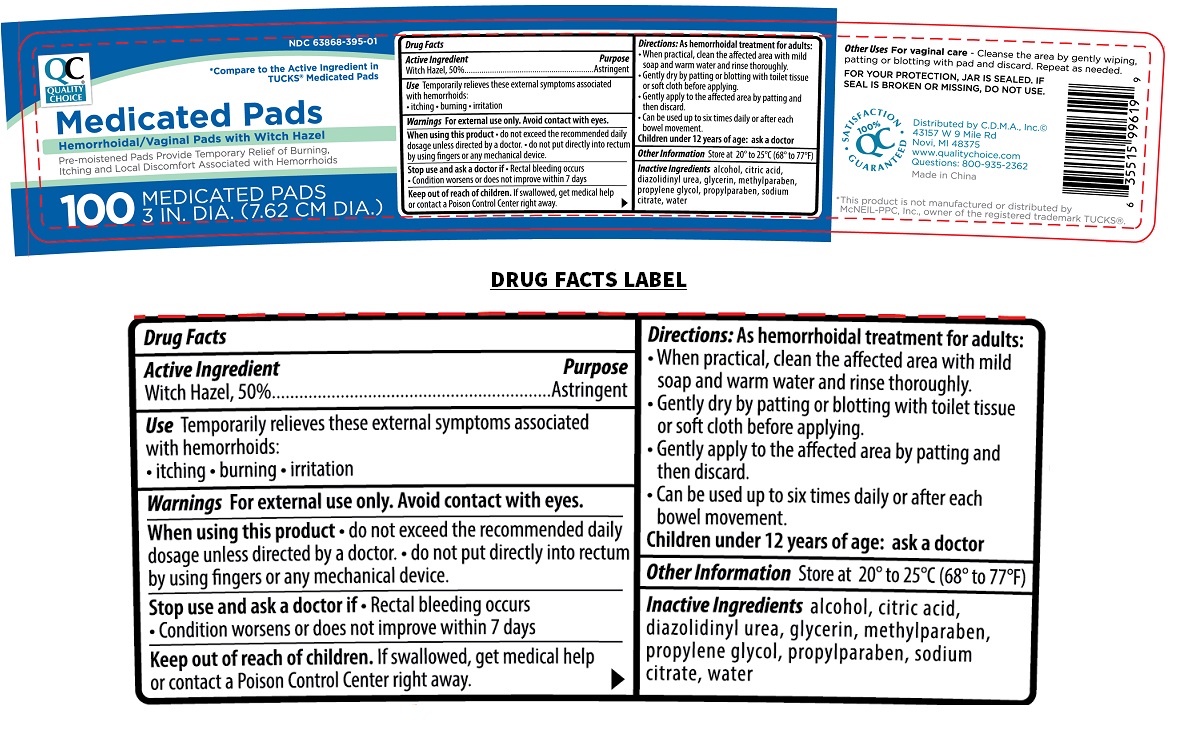 DRUG LABEL: Quality Choice Medicated Pads
NDC: 63868-395 | Form: CLOTH
Manufacturer: QUALITY CHOICE (Chain Drug Marketing Association)
Category: otc | Type: HUMAN OTC DRUG LABEL
Date: 20230109

ACTIVE INGREDIENTS: WITCH HAZEL 0.0086 g/1 1
INACTIVE INGREDIENTS: ALCOHOL; CITRIC ACID MONOHYDRATE; DIAZOLIDINYL UREA; GLYCERIN; METHYLPARABEN; PROPYLENE GLYCOL; PROPYLPARABEN; SODIUM CITRATE, UNSPECIFIED FORM; WATER

QUALITY CHOICE Medicated Pads

Active Ingredient

Witch Hazel, 50%

Purpose

Astringent

Use

Temporarily relieves these external symptoms associated with hemorrhoids:
• itching • burning • irritation

Warnings

For external use only. Avoid contact with eyes.

When using this product • do not exceed the recommended daily dosage unless directed by a doctor. • do not put directly into rectum by using fingers or any mechanical device.

Stop use and ask a doctor if • Rectal bleeding occurs • Condition worsens or does not improve within 7 days

Keep out of reach of children. If swallowed, get medical help or contact a Poison Control Center right away.

Directions:

As hemorrhoidal treatment for adults:
• When practical, clean the affected area with mild soap and warm water and rinse thoroughly.
• Gently dry by patting or blotting with toilet tissue or soft cloth before applying.
• Gently apply to the affected area by patting and then discard.
• Can be used up to six times daily or after each bowel movement.
Children under 12 years of age: ask a doctor

Other Information

Store at 20° to 25°C (68° to 77°F)

Inactive Ingredients

alcohol, citric acid, diazolidinyl urea, glycerin, methylparaben, propylene glycol, propylparaben, sodium citrate, water

* Compare to the Active Ingredient in TUCKS® Medicated pads

Hemorrhoidal/Vaginal pads with Witch Hazel

Pre-moistened Pads Provide Temporary Relief of Burning, Itching and Local Discomfort Associated with Hemorrhoids

Other Uses For vaginal care - Cleanse the area by gently wiping, patting or blotting with pad and discard. Repeat as needed.

FOR YOUR PROTECTION, JAR IS SEALED. IF SEAL IS BROKEN OR MISSING, DO NOT USE.

• SATISFACTION • GUARANTEED 100% QC

Distributed by C.D.M.A., Inc.©
43157 W 9 Mile Rd
Novi, MI 48375
www.qualitychoice.com
Questions: 800-935-2362

Made in China

*This product is not manufactured or distributed by McNEIL-PPC, Inc., owner of the registered trademark TUCKS®.